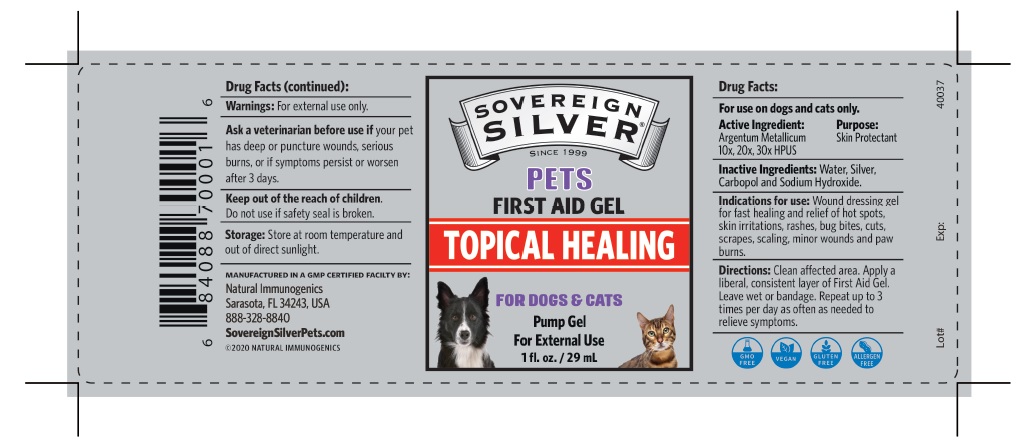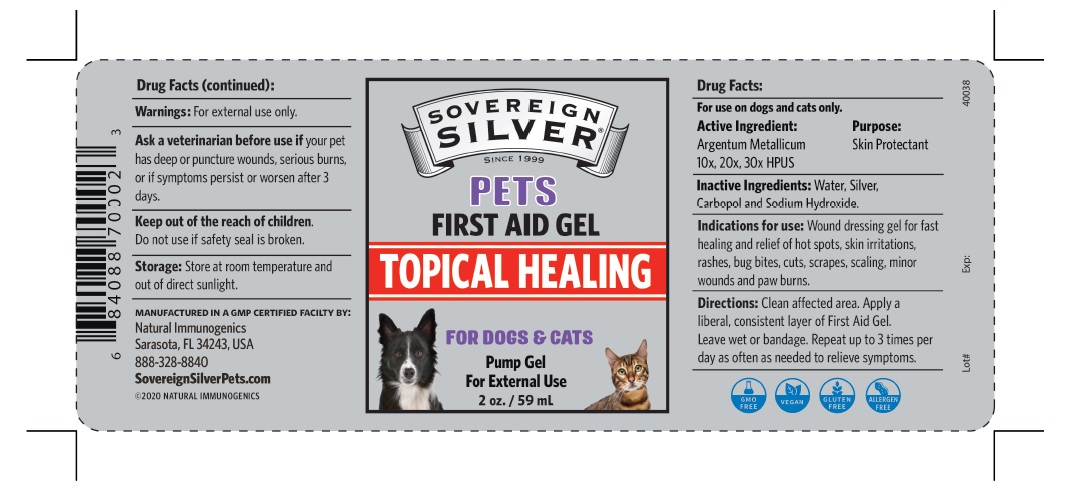 DRUG LABEL: Sovereign Silver
NDC: 52166-013 | Form: GEL
Manufacturer: Natural Immunogenics Corp.dba SOVEREIGN NATURALS
Category: animal | Type: OTC ANIMAL DRUG LABEL
Date: 20250521

ACTIVE INGREDIENTS: SILVER 30 [hp_X]/1 mL
INACTIVE INGREDIENTS: WATER; CARBOMER HOMOPOLYMER TYPE B (ALLYL PENTAERYTHRITOL CROSSLINKED); SODIUM HYDROXIDE

Active ingredient Purpose

Argentum Metallicum Skin Protectant

10x, 20x, 30x HPUS

Inactive Ingredients

Water, Silver, Carbopol and Sodium Hydroxide.

Indications for use

Wound dressing gel for fast healing and relief of hot spots, skin irritations, rashes, bug bites, cuts, scrapes, scaling, minor wounds and paw
burns.

Directions

Clean affected area. Apply a liberal, consistent layer of First Aid Gel. Leave wet or bandage. Repeat up to 3 times per day as often as needed to
relieve symptoms.

Warnings: For external use only.

Ask a veterinarian before use if your pet has deep or puncture wounds, open sores, serious burns, or if symptoms persist or worsen after 3 days.

Keep out of reach of children.

Do not use if seal is broken.

Storage: Store at room temperature and out of direct sunlight.